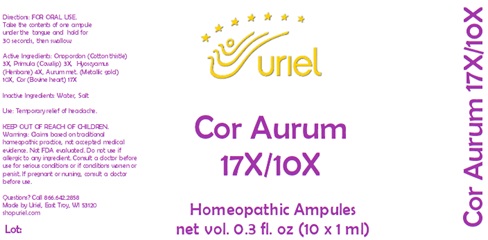 DRUG LABEL: Cor Aurum 17/10
NDC: 48951-3127 | Form: LIQUID
Manufacturer: Uriel Pharmacy Inc.
Category: homeopathic | Type: HUMAN OTC DRUG LABEL
Date: 20231030

ACTIVE INGREDIENTS: ONOPORDUM ACANTHIUM FLOWER 3 [hp_X]/1 mL; PRIMULA VERIS FLOWER 3 [hp_X]/1 mL; HYOSCYAMUS NIGER LEAF 4 [hp_X]/1 mL; GOLD 10 [hp_X]/1 mL; BEEF HEART 17 [hp_X]/1 mL
INACTIVE INGREDIENTS: WATER; SODIUM CHLORIDE

Cor Aurum 17/10

INDICATIONS AND USAGE

Directions: FOR ORAL USE.

DOSAGE AND ADMINISTRATION

Take the contents of one ampule under the tongue and hold for 30 seconds, then swallow.

ACTIVE INGREDIENT

Active Ingredients: Onopordon (Cotton thistle) 3X, Primula (Cowslip) 3X, Hyoscyamus (Henbane) 4X, Aurum met. (Metallic gold) 10X, Cor (Bovine heart) 17X

Inactive Ingredients: Water, Salt

PURPOSE

Use: Temporary relief of headache.

KEEP OUT OF REACH OF CHILDREN.

WARNINGS

Warnings: Claims based on traditional homeopathic practice, not accepted medical evidence. Not FDA evaluated. Do not use if allergic to any ingredient. Consult a doctor before use for serious conditions or if conditions worsen or persist. If pregnant or nursing, consult a doctor before use.

Questions? Call 866.642.2858

Made by Uriel, East Troy, WI 53120

shopuriel.com